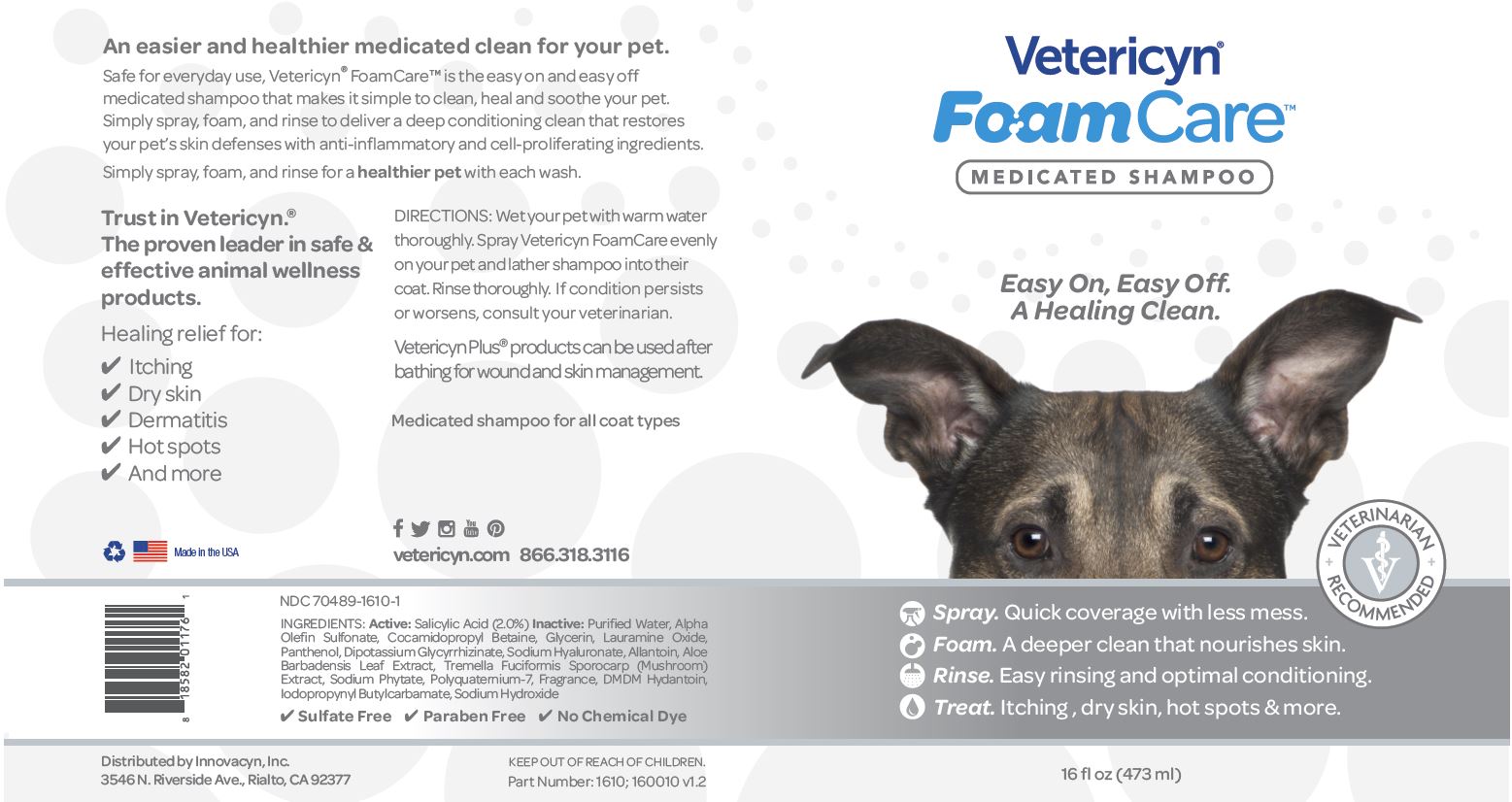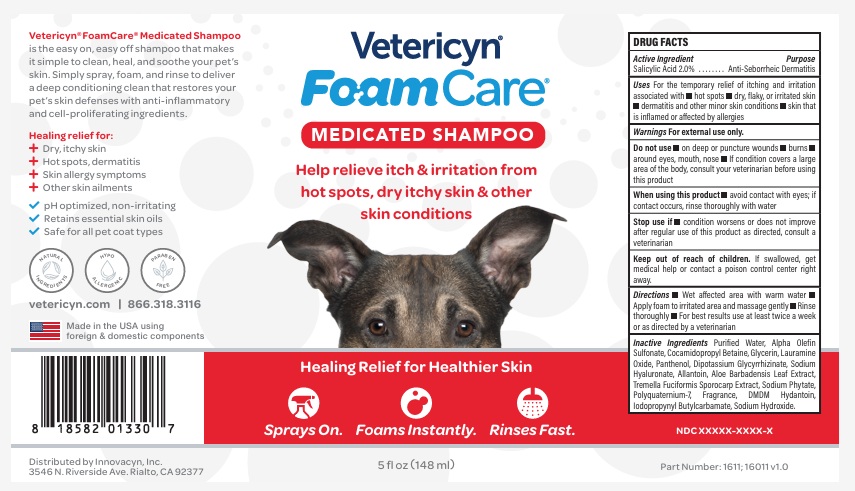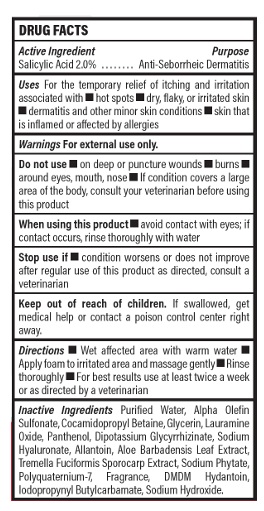 DRUG LABEL: Vetericyn FoamCare
NDC: 70489-1610 | Form: SHAMPOO
Manufacturer: Innovacyn Inc.
Category: animal | Type: OTC ANIMAL DRUG LABEL
Date: 20260219

ACTIVE INGREDIENTS: SALICYLIC ACID 20 mg/1 mL
INACTIVE INGREDIENTS: WATER; SODIUM C14-16 OLEFIN SULFONATE; COCAMIDOPROPYL BETAINE; GLYCERIN ; LAURAMINE OXIDE; PANTHENOL ; ENOXOLONE DIPOTASSIUM; HYALURONATE SODIUM ; ALLANTOIN; ALOE VERA LEAF; TREMELLA FUCIFORMIS FRUITING BODY; PHYTATE SODIUM; POLYQUATERNIUM-7 (70/30 ACRYLAMIDE/DADMAC; 1600000 MW); DMDM HYDANTOIN; IODOPROPYNYL BUTYLCARBAMATE; SODIUM HYDROXIDE

Package Labeling

ACTIVE INGREDIENT

NDC:70489-1610-1

INGREDIENTS:

Active: Salicylic Acid (2.0%)

Inactive: Purified Water, Alpha Olefin Sulfonate, Cocamidopropyl Betaine, Glycerin, Lauramine Oxide, Panthenol, Dipotassion Glycyrrhizinate, Sodium Hyaluronate, Allantoin, Aloe Barbadensis Leaf Extract, Tremella Fuciformis Sporocarp (Mushroom) Extract, Sodium Phytate, Polyquaternium-7, Fragrance, DMDM Hydantoin, Iodopropynyl Butylcarbamate, Sodium Hydroxide

Sulfate Free Paraben Free No Chemical dye

DESCRIPTION

An easier and healthier medicated clean for your pet.

Safe for everyday use, Vetericyn FoamCare is the easy on and easy off medicated shampoo that makes it simple to clean, heal, and sooth your pet. Simply spray,foam, and rinse to deliver a deep-conditioning clean that restores your pet's skin defenses with anti-inflammatory and cell-proliferating ingredients.

Simply spray, foam, and rinse for a healthier pet with each wash.

Trust in Vetericyn. The proven leader in safe and effective animal wellness products.

Healing relief for:

Itching

Dry skin

Dermatitis

Hot spots

And more

Logo Recycle Logo U.S. Flag Made in the USA

DIRECTIONS:

Wet your pet with warm water thoroughly.

Spray Vetericyn FoamCare evenly on your pet and lather shampoo into the coat.

Rinse thoroughly.

GENERAL PRECAUTIONS

If condition persists or worsens, consult your veterinarian.

Vetericyn Plus products can be used after bathing for wound and skin management.

Medicated shampoo for all coat types

QUESTIONS

vetericyn.com 866.318.3116

KEEP OUT OF REACH OF CHILDREN.

PACKAGE LABEL

Vetericyn

FoamCare

MEDICATED SHAMPOO

Easy On, Easy Off.

A Healing Clean.

Logo VETERINARIAN RECOMMENDED

Logo Spray. Quick coverage with less mess.

Logo Foam. A deeper clean that nourishes skin.

Logo Rinse. Easy rinsing and optimal conditioning.

Logo Treat. Itching, dry skin. hot spots and more.

16 fl oz (473 ml)